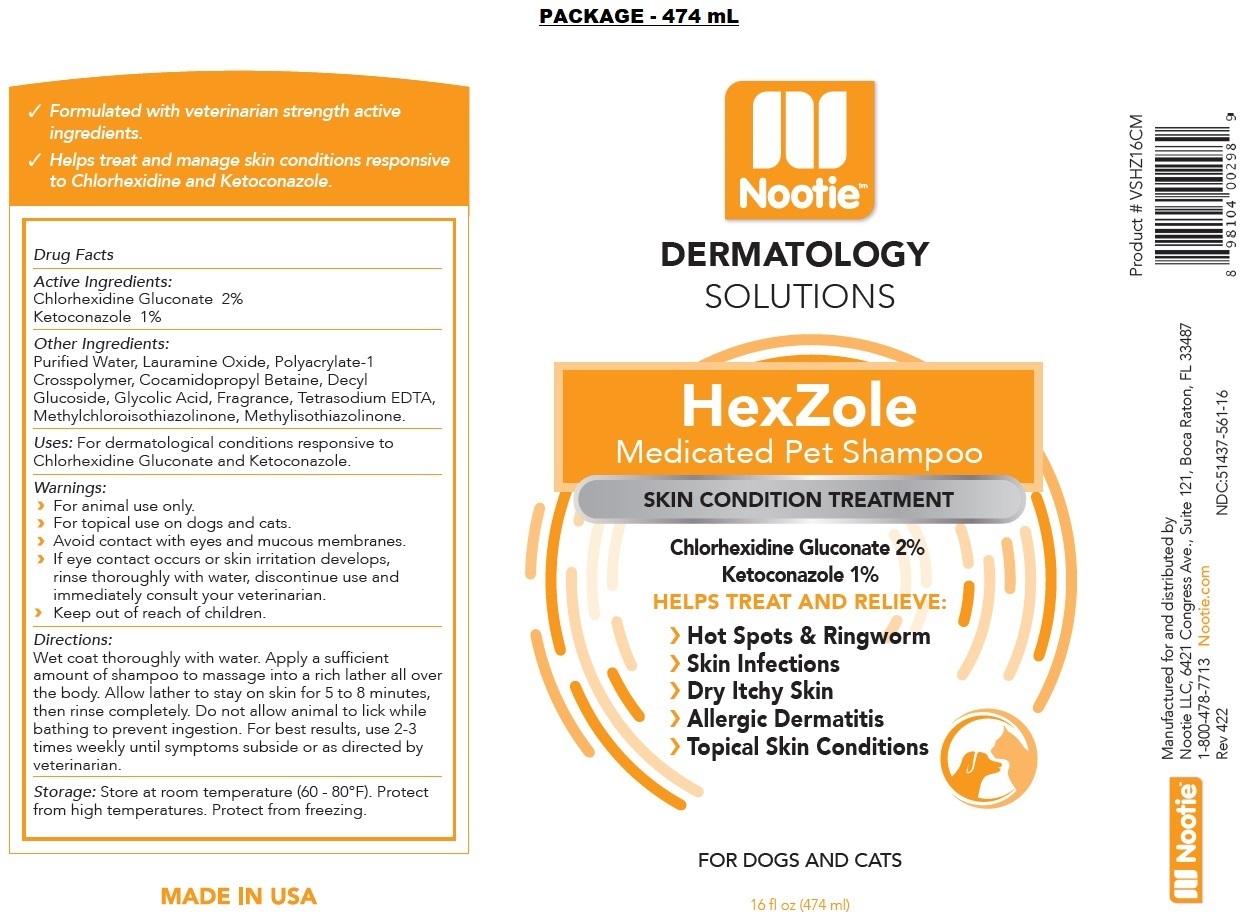 DRUG LABEL: Nootie
NDC: 51437-561 | Form: SHAMPOO
Manufacturer: Nootie LLC
Category: animal | Type: OTC ANIMAL DRUG LABEL
Date: 20221207

ACTIVE INGREDIENTS: CHLORHEXIDINE GLUCONATE 2 g/100 mL; KETOCONAZOLE 1 g/100 mL
INACTIVE INGREDIENTS: WATER; LAURAMINE OXIDE; POLYACRYLATE-1 CROSSPOLYMER; COCAMIDOPROPYL BETAINE; DECYL GLUCOSIDE; GLYCOLIC ACID; EDETATE SODIUM; METHYLCHLOROISOTHIAZOLINONE; METHYLISOTHIAZOLINONE

Nootie™ HexZole Medicated Pet Shampoo

Active Ingredients:

Chlorhexidine Gluconate 2%

Ketoconazole 1%

Other Ingredients:

Purified Water, Lauramine Oxide, Polyacrylate-1 Crosspolymer, Cocamidopropyl Betaine, Decyl Glucoside, Glycolic Acid, Fragrance, Tetrasodium EDTA, Methylchloroisothiazolinone, Methylisothiazolinone.

Uses:

For dermatological conditions responsive to Chlorhexidine Gluconate and Ketoconazole.

Warnings:

› For animal use only.
› For topical use on dogs and cats.
› Avoid contact with eyes and mucous membranes.
› If eye contact occurs or skin irritation develops, rinse thoroughly with water, discontinue use and immediately consult your veterinarian.
› Keep out of reach of children.

Directions:

Wet coat thoroughly with water. Apply a sufficient amount of shampoo to massage into a rich lather all over the body. Allow lather to stay on skin for 5 to 8 minutes, then rinse completely. Do not allow animal to lick while bathing to prevent ingestion. For best results, use 2-3 times weekly until symptoms subside or as directed by veterinarian.

Storage:

Store at room temperature (60 - 80°F). Protect from high temperatures. Protect from freezing.

Nootie™ DERMATOLOGY SOLUTIONS

SKIN CONDITION TREATMENT

HELPS TREAT AND RELIEVE:

› Hot Spots & Ringworm
› Skin Infections
› Dry Itchy Skin
› Allergic Dermatitis
› Topical Skin Conditions

FOR DOGS AND CATS

√ Formulated with veterinarian strength active ingredients.
√ Helps treat and manage skin conditions responsive to Chlorhexidine and Ketoconazole.

MADE IN USA

Manufactured for and distributed by
Nootie LLC, 6421 Congress Ave., Suite 121, Boca Raton, FL 33487
1-800-478-7713 Nootie.com